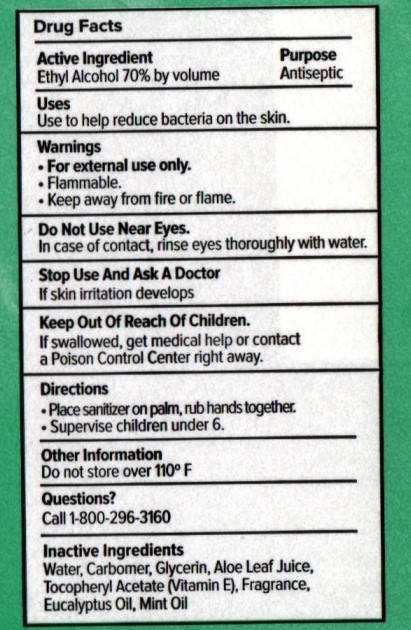 DRUG LABEL: Moxe Hand Sanitizer Eucalyptus Mint
NDC: 84004-002 | Form: GEL
Manufacturer: Premark Health Science
Category: otc | Type: HUMAN OTC DRUG LABEL
Date: 20250430

ACTIVE INGREDIENTS: ALCOHOL 70 mL/100 mL
INACTIVE INGREDIENTS: .ALPHA.-TOCOPHEROL ACETATE, DL-; GLYCERIN; EUCALYPTUS OIL; WATER; ALOE; CARBOMER HOMOPOLYMER, UNSPECIFIED TYPE

Moxe Eucalyptus Mint Hand Sanitizer